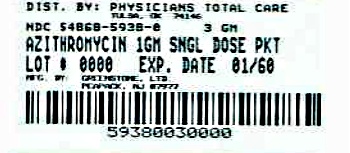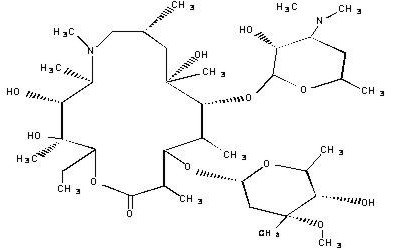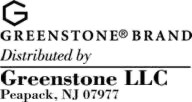 DRUG LABEL: azithromycin
NDC: 54868-5938 | Form: POWDER, FOR SUSPENSION
Manufacturer: Physicians Total Care, Inc.
Category: prescription | Type: HUMAN PRESCRIPTION DRUG LABEL
Date: 20120529

ACTIVE INGREDIENTS: AZITHROMYCIN DIHYDRATE 1 g/1 1
INACTIVE INGREDIENTS: silicon dioxide; sodium phosphate, tribasic anhydrous; sucrose

AZITHROMYCIN
azithromycin tablets
and
azithromycin for oral suspension

To reduce the development of drug-resistant bacteria and maintain the effectiveness of azithromycin and other antibacterial drugs, azithromycin should be used only to treat or prevent infections that are proven or strongly suspected to be caused by bacteria.

DESCRIPTION

Azithromycin tablets and azithromycin for oral suspension contain the active ingredient azithromycin, an azalide, a subclass of macrolide antibiotics, for oral administration. Azithromycin has the chemical name (2R,3S,4R,5R,8R,10R,11R,12S,13S,14R)-13-[(2,6-dideoxy-3-C-methyl-3-O-methyl-α-L-ribo-hexopyranosyl)oxy]-2-ethyl-3,4,10-trihydroxy-3,5,6,8,10,12,14-heptamethyl-11-[[3,4,6-trideoxy-3-(dimethylamino)-β-D-xylo-hexopyranosyl]oxy]-1-oxa-6-azacyclopentadecan-15-one. Azithromycin is derived from erythromycin; however, it differs chemically from erythromycin in that a methyl-substituted nitrogen atom is incorporated into the lactone ring. Its molecular formula is C38H72N2O12, and its molecular weight is 749.0. Azithromycin has the following structural formula:

Azithromycin, as the dihydrate, is a white crystalline powder with a molecular formula of C38H72N2O12•2H2O and a molecular weight of 785.0.

Azithromycin tablets contain azithromycin dihydrate equivalent to 600 mg azithromycin. The tablets are supplied as white, modified oval-shaped, film-coated tablets. They also contain the following inactive ingredients: dibasic calcium phosphate anhydrous, pregelatinized starch, sodium croscarmellose, magnesium stearate, sodium lauryl sulfate and an aqueous film coat consisting of hypromellose, titanium dioxide, lactose and triacetin.

Azithromycin for oral suspension is supplied in a single dose packet containing azithromycin dihydrate equivalent to 1 g azithromycin. It also contains the following inactive ingredients: colloidal silicon dioxide, sodium phosphate tribasic, anhydrous; spray dried artificial banana flavor, spray dried artificial cherry flavor, and sucrose.

CLINICAL PHARMACOLOGY

Pharmacokinetics

Following oral administration, azithromycin is rapidly absorbed and widely distributed throughout the body. Rapid distribution of azithromycin into tissues and high concentration within cells result in significantly higher azithromycin concentrations in tissues than in plasma or serum. The 1 g single dose packet is bioequivalent to four 250 mg azithromycin capsules.

The pharmacokinetic parameters of azithromycin in plasma after dosing as per labeled recommendations in healthy young adults and asymptomatic HIV-seropositive adults (age 18–40 years old) are portrayed in the following chart:

MEAN (CV%) PK PARAMETER
DOSE/DOSAGE FORM (serum, except as indicated) | Subjects | Day No. | Cmax (µg/mL) | Tmax (hr) | C24 (µg/mL) | AUC (µg∙hr/mL) | T½ (hr) | Urinary Excretion (% of dose)
500 mg/250 mg capsule | 12 | Day 1 | 0.41 | 2.5 | 0.05 | 2.6 [AUC0–24;] | – | 4.5
and 250 mg on Days 2–5 | 12 | Day 5 | 0.24 | 3.2 | 0.05 | 2.1 | – | 6.5
1200 mg/600 mg tablets | 12 | Day 1 | 0.66 | 2.5 | 0.074 | 6.8 [0–last.] | 40 | –
%CV |  |  | (62%) | (79%) | (49%) | (64%) | (33%)
600 mg tablet/day | 7 | 1 | 0.33 | 2.0 | 0.039 | 2.4
%CV |  |  | 25% | (50%) | (36%) | (19%)
 | 7 | 22 | 0.55 | 2.1 | 0.14 | 5.8 | 84.5 | -
%CV |  |  | (18%) | (52%) | (26%) | (25%) |  | -
600 mg tablet/day (leukocytes) | 7 | 22 | 252 | 10.9 | 146 | 4763 | 82.8 | -
%CV |  |  | (49%) | (28%) | (33%) | (42%) | - | -

In these studies (500 mg Day 1, 250 mg Days 2–5), there was no significant difference in the disposition of azithromycin between male and female subjects. Plasma concentrations of azithromycin following single 500 mg oral and I.V. doses declined in a polyphasic pattern resulting in an average terminal half-life of 68 hours. With a regimen of 500 mg on Day 1 and 250 mg/day on Days 2–5, Cmin and Cmax remained essentially unchanged from Day 2 through Day 5 of therapy. However, without a loading dose, azithromycin Cmin levels required 5 to 7 days to reach steady-state.

In asymptomatic HIV-seropositive adult subjects receiving 600-mg azithromycin tablets once daily for 22 days, steady state azithromycin serum levels were achieved by Day 15 of dosing.

When azithromycin capsules were administered with food, the rate of absorption (Cmax) of azithromycin was reduced by 52% and the extent of absorption (AUC) by 43%.

When the oral suspension of azithromycin was administered with food, the Cmax increased by 46% and the AUC by 14%.

The absolute bioavailability of two 600 mg tablets was 34% (CV=56%). Administration of two 600 mg tablets with food increased Cmax by 31% (CV=43%) while the extent of absorption (AUC) was unchanged (mean ratio of AUCs=1.00; CV=55%).

The AUC of azithromycin in 250 mg capsules was unaffected by coadministration of an antacid containing aluminum and magnesium hydroxide with azithromycin; however, the Cmax was reduced by 24%. Administration of cimetidine (800 mg) two hours prior to azithromycin had no effect on azithromycin absorption.

When studied in healthy elderly subjects from age 65 to 85 years, the pharmacokinetic parameters of azithromycin (500 mg Day 1, 250 mg Days 2–5) in elderly men were similar to those in young adults; however, in elderly women, although higher peak concentrations (increased by 30 to 50%) were observed, no significant accumulation occurred.

The high values in adults for apparent steady-state volume of distribution (31.1 L/kg) and plasma clearance (630 mL/min) suggest that the prolonged half-life is due to extensive uptake and subsequent release of drug from tissues. Selected tissue (or fluid) concentration and tissue (or fluid) to plasma/serum concentration ratios are shown in the following table:

AZITHROMYCIN CONCENTRATIONS FOLLOWING TWO 250 mg (500 mg) CAPSULES IN ADULTS
TISSUE OR FLUID | TIME AFTER DOSE (h) | TISSUE OR FLUID CONCENTRATION (µg/g or µg/mL) [High tissue concentrations should not be interpreted to be quantitatively related to clinical efficacy. The antimicrobial activity of azithromycin is pH related. Azithromycin is concentrated in cell lysosomes which have a low intraorganelle pH, at which the drug's activity is reduced. However, the extensive distribution of drug to tissues may be relevant to clinical activity.] | CORRESPONDING PLASMA OR SERUM LEVEL (µg/mL) | TISSUE (FLUID) PLASMA (SERUM) RATIO
SKIN | 72–96 | 0.4 | 0.012 | 35
LUNG | 72–96 | 4.0 | 0.012 | >100
SPUTUM [Sample was obtained 2–4 hours after the first dose] | 2–4 | 1.0 | 0.64 | 2
SPUTUM [Sample was obtained 10–12 hours after the first dose.] | 10–12 | 2.9 | 0.1 | 30
TONSIL [Dosing regimen of 2 doses of 250 mg each, separated by 12 hours.] | 9–18 | 4.5 | 0.03 | >100
TONSIL | 180 | 0.9 | 0.006 | >100
CERVIX [Sample was obtained 19 hours after a single 500 mg dose.] | 19 | 2.8 | 0.04 | 70

The extensive tissue distribution was confirmed by examination of additional tissues and fluids (bone, ejaculum, prostate, ovary, uterus, salpinx, stomach, liver, and gallbladder). As there are no data from adequate and well-controlled studies of azithromycin treatment of infections in these additional body sites, the clinical significance of these tissue concentration data is unknown.

Following a regimen of 500 mg on the first day and 250 mg daily for 4 days, only very low concentrations were noted in cerebrospinal fluid (less than 0.01 µg/mL) in the presence of non-inflamed meninges.

Following oral administration of a single 1200 mg dose (two 600 mg tablets), the mean maximum concentration in peripheral leukocytes was 140 µg/mL. Concentrations remained above 32 µg/mL for approximately 60 hr. The mean half-lives for 6 males and 6 females were 34 hr and 57 hr, respectively. Leukocyte to plasma Cmax ratios for males and females were 258 (±77%) and 175 (±60%), respectively, and the AUC ratios were 804 (±31%) and 541 (±28%), respectively. The clinical relevance of these findings is unknown.

Following oral administration of multiple daily doses of 600 mg (1 tablet/day) to asymptomatic HIV-seropositive adults, mean maximum concentration in peripheral leukocytes was 252 µg/mL (±49%). Trough concentrations in peripheral leukocytes at steady-state averaged 146 µg/mL (±33%). The mean leukocyte to serum Cmax ratio was 456 (±38%) and the mean leukocyte to serum AUC ratio was 816 (±31%). The clinical relevance of these findings is unknown.

The serum protein binding of azithromycin is variable in the concentration range approximating human exposure, decreasing from 51% at 0.02 µg/mL to 7% at 2 µg/mL. Biliary excretion of azithromycin, predominantly as unchanged drug, is a major route of elimination. Over the course of a week, approximately 6% of the administered dose appears as unchanged drug in urine.

Renal Insufficiency

Azithromycin pharmacokinetics was investigated in 42 adults (21 to 85 years of age) with varying degrees of renal impairment. Following the oral administration of a single 1.0 g dose of azithromycin (4 × 250 mg capsules), the mean Cmax and AUC0–120 increased by 5.1% and 4.2%, respectively in subjects with GFR 10 to 80 mL/min compared to subjects with normal renal function (GFR >80 mL/min). The mean Cmax and AUC0–120 increased 61% and 35%, respectively in subjects with end-stage renal disease (GFR <10 mL/min) compared to subjects with normal renal function (GFR >80 mL/min). (See DOSAGE AND ADMINISTRATION.)

Hepatic Insufficiency

The pharmacokinetics of azithromycin in subjects with hepatic impairment has not been established.

The effect of azithromycin on the plasma levels or pharmacokinetics of theophylline administered in multiple doses adequate to reach therapeutic steady-state plasma levels is not known. (See PRECAUTIONS.)

Mechanism of Action

Azithromycin acts by binding to the 50S ribosomal subunit of susceptible microorganisms and, thus, interfering with microbial protein synthesis. Nucleic acid synthesis is not affected.

Azithromycin concentrates in phagocytes and fibroblasts as demonstrated by in vitro incubation techniques. Using such methodology, the ratio of intracellular to extracellular concentration was >30 after one hour incubation. In vivo studies suggest that concentration in phagocytes may contribute to drug distribution to inflamed tissues.

Microbiology

Azithromycin has been shown to be active against most strains of the following microorganisms, both in vitro and in clinical infections as described in the INDICATIONS AND USAGE section.

Aerobic Gram-Positive Microorganisms

Staphylococcus aureus
Streptococcus agalactiae
Streptococcus pneumoniae
Streptococcus pyogenes

NOTE: Azithromycin demonstrates cross-resistance with erythromycin-resistant gram-positive strains. Most strains of Enterococcus faecalis and methicillin-resistant staphylococci are resistant to azithromycin.

Aerobic Gram-Negative Microorganisms

Haemophilus influenzae
Moraxella catarrhalis

"Other" Microorganisms

Chlamydia trachomatis

Beta-lactamase production should have no effect on azithromycin activity.

Azithromycin has been shown to be active in vitro and in the prevention and treatment of disease caused by the following microorganisms:

Mycobacteria

Mycobacterium avium complex (MAC) consisting of:
Mycobacterium avium
Mycobacterium intracellulare.

The following in vitro data are available, but their clinical significance is unknown.

Azithromycin exhibits in vitro minimal inhibitory concentrations (MICs) of 2.0 µg/mL or less against most (≥90%) strains of the following microorganisms; however, the safety and effectiveness of azithromycin in treating clinical infections due to these microorganisms have not been established in adequate and well-controlled trials.

Aerobic Gram-Positive Microorganisms

Streptococci (Groups C, F, G)
Viridans group streptococci

Aerobic Gram-Negative Microorganisms

Bordetella pertussis
Campylobacter jejuni
Haemophilus ducreyi
Legionella pneumophila

Anaerobic Microorganisms

Bacteroides bivius
Clostridium perfringens
Peptostreptococcus species

"Other" Microorganisms

Borrelia burgdorferi
Mycoplasma pneumoniae
Treponema pallidum
Ureaplasma urealyticum

Susceptibility Testing of Bacteria Excluding Mycobacteria

The in vitro potency of azithromycin is markedly affected by the pH of the microbiological growth medium during incubation. Incubation in a 10% CO2 atmosphere will result in lowering of media pH (7.2 to 6.6) within 18 hours and in an apparent reduction of the in vitro potency of azithromycin. Thus, the initial pH of the growth medium should be 7.2–7.4, and the CO2 content of the incubation atmosphere should be as low as practical.

Azithromycin can be solubilized for in vitro susceptibility testing by dissolving in a minimum amount of 95% ethanol and diluting to working concentration with water.

Dilution Techniques

Quantitative methods are used to determine minimal inhibitory concentrations that provide reproducible estimates of the susceptibility of bacteria to antimicrobial compounds. One such standardized procedure uses a standardized dilution method^1 (broth, agar or microdilution) or equivalent with azithromycin powder. The MIC values should be interpreted according to the following criteria:

MIC (µg/mL) | Interpretation
≤ 2 | Susceptible (S)
4 | Intermediate (I)
≥ 8 | Resistant (R)

A report of "Susceptible" indicates that the pathogen is likely to respond to monotherapy with azithromycin. A report of "Intermediate" indicates that the result should be considered equivocal, and, if the microorganism is not fully susceptible to alternative, clinically feasible drugs, the test should be repeated. This category also provides a buffer zone which prevents small uncontrolled technical factors from causing major discrepancies in interpretation. A report of "Resistant" indicates that usually achievable drug concentrations are unlikely to be inhibitory and that other therapy should be selected.

Measurement of MIC or MBC and achieved antimicrobial compound concentrations may be appropriate to guide therapy in some infections. (See CLINICAL PHARMACOLOGY section for further information on drug concentrations achieved in infected body sites and other pharmacokinetic properties of this antimicrobial drug product.)

Standardized susceptibility test procedures require the use of laboratory control microorganisms. Standard azithromycin powder should provide the following MIC values:

Microorganism | MIC (µg/mL)
Escherichia coli ATCC 25922 | 2.0–8.0
Enterococcus faecalis ATCC 29212 | 1.0–4.0
Staphylococcus aureus ATCC 29213 | 0.25–1.0

Diffusion Techniques

Quantitative methods that require measurement of zone diameters also provide reproducible estimates of the susceptibility of bacteria to antimicrobial compounds. One such standardized procedure^2 that has been recommended for use with disks to test the susceptibility of microorganisms to azithromycin uses the 15-µg azithromycin disk. Interpretation involves the correlation of the diameter obtained in the disk test with the minimal inhibitory concentration (MIC) for azithromycin.

Reports from the laboratory providing results of the standard single-disk susceptibility test with a 15 µg azithromycin disk should be interpreted according to the following criteria:

Zone Diameter (mm) | Interpretation
≥ 18 | (S) Susceptible
14–17 | (I) Intermediate
≤ 13 | (R) Resistant

Interpretation should be as stated above for results using dilution techniques.

As with standardized dilution techniques, diffusion methods require the use of laboratory control microorganisms. The 15-µg azithromycin disk should provide the following zone diameters in these laboratory test quality control strains:

Microorganism | Zone Diameter (mm)
Staphylococcus aureus ATCC 25923 | 21–26

In Vitro Activity of Azithromycin Against Mycobacteria

Azithromycin has demonstrated in vitro activity against Mycobacterium avium complex (MAC) organisms. While gene probe techniques may be used to distinguish between M. avium and M. intracellulare, many studies only reported results on M. avium complex (MAC) isolates. Azithromycin has also been shown to be active against phagocytized M. avium complex (MAC) organisms in mouse and human macrophage cell cultures as well as in the beige mouse infection model.

Various in vitro methodologies employing broth or solid media at different pHs, with and without oleic acid-albumin dextrose-catalase (OADC), have been used to determine azithromycin MIC values for Mycobacterium avium complex strains. In general, azithromycin MIC values decreased 4 to 8 fold as the pH of Middlebrook 7H11 agar media increased from 6.6 to 7.4. At pH 7.4, azithromycin MIC values determined with Mueller-Hinton agar were 4 fold higher than that observed with Middlebrook 7H12 media at the same pH. Utilization of oleic acid-albumin-dextrose-catalase (OADC) in these assays has been shown to further alter MIC values. The relationship between azithromycin and clarithromycin MIC values has not been established. In general, azithromycin MIC values were observed to be 2 to 32 fold higher than clarithromycin independent of the susceptibility method employed.

The ability to correlate MIC values and plasma drug levels is difficult as azithromycin concentrates in macrophages and tissues. (See CLINICAL PHARMACOLOGY)

Drug Resistance

Complete cross-resistance between azithromycin and clarithromycin has been observed with Mycobacterium avium complex (MAC) isolates. In most isolates, a single point mutation at a position that is homologous to the Escherichia coli positions 2058 or 2059 on the 23S rRNA gene is the mechanism producing this cross-resistance pattern.^3,4 Mycobacterium avium complex (MAC) isolates exhibiting cross-resistance show an increase in azithromycin MICs to ≥128 µg/mL with clarithromycin MICs increasing to ≥32 µg/mL. These MIC values were determined employing the radiometric broth dilution susceptibility testing method with Middlebrook 7H12 medium. The clinical significance of azithromycin and clarithromycin cross-resistance is not fully understood at this time but preclinical data suggest that reduced activity to both agents will occur after M. avium complex strains produce the 23S rRNA mutation.

Susceptibility testing for Mycobacterium avium complex (MAC)

The disk diffusion techniques and dilution methods for susceptibility testing against Gram-positive and Gram-negative bacteria should not be used for determining azithromycin MIC values against mycobacteria. In vitro susceptibility testing methods and diagnostic products currently available for determining minimal inhibitory concentration (MIC) values against Mycobacterium avium complex (MAC) organisms have not been standardized or validated. Azithromycin MIC values will vary depending on the susceptibility testing method employed, composition and pH of media and the utilization of nutritional supplements. Breakpoints to determine whether clinical isolates of M. avium or M. intracellulare are susceptible or resistant to azithromycin have not been established.

The clinical relevance of azithromycin in vitro susceptibility test results for other mycobacterial species, including Mycobacterium tuberculosis, using any susceptibility testing method has not been determined.

INDICATIONS AND USAGE

Azithromycin is indicated for the treatment of patients with mild to moderate infections caused by susceptible strains of the designated microorganisms in the specific conditions listed below.

Sexually Transmitted Diseases

Non-gonococcal urethritis and cervicitis due to Chlamydia trachomatis.

Azithromycin at the recommended dose, should not be relied upon to treat gonorrhea or syphilis. Antimicrobial agents used in high doses for short periods of time to treat non-gonococcal urethritis may mask or delay the symptoms of incubating gonorrhea or syphilis. All patients with sexually-transmitted urethritis or cervicitis should have a serologic test for syphilis and appropriate cultures for gonorrhea performed at the time of diagnosis. Appropriate antimicrobial therapy and follow-up tests for these diseases should be initiated if infection is confirmed.

Appropriate culture and susceptibility tests should be performed before treatment to determine the causative organism and its susceptibility to azithromycin. Therapy with azithromycin may be initiated before results of these tests are known; once the results become available, antimicrobial therapy should be adjusted accordingly.

To reduce the development of drug-resistant bacteria and maintain the effectiveness of azithromycin and other antibacterial drugs, azithromycin should be used only to treat or prevent infections that are proven or strongly suspected to be caused by susceptible bacteria. When culture and susceptibility information are available, they should be considered in selecting or modifying antibacterial therapy. In the absence of such data, local epidemiology and susceptibility patterns may contribute to the empiric selection of therapy.

Mycobacterial Infections

Prophylaxis of Disseminated Mycobacterium avium complex (MAC) Disease

Azithromycin taken alone or in combination with rifabutin at its approved dose, is indicated for the prevention of disseminated Mycobacterium avium complex (MAC) disease in persons with advanced HIV infection. (See DOSAGE AND ADMINISTRATION, CLINICAL STUDIES)

Treatment of Disseminated Mycobacterium avium complex (MAC) Disease

Azithromycin taken in combination with ethambutol, is indicated for the treatment of disseminated MAC infections in persons with advanced HIV infection. (See DOSAGE AND ADMINISTRATION, CLINICAL STUDIES)

CONTRAINDICATIONS

Azithromycin is contraindicated in patients with known hypersensitivity to azithromycin, erythromycin, any macrolide or ketolide antibiotic.

WARNINGS

Serious allergic reactions, including angioedema, anaphylaxis, and dermatologic reactions including Stevens Johnson Syndrome and toxic epidermal necrolysis have been reported rarely in patients on azithromycin therapy. Although rare, fatalities have been reported (see CONTRAINDICATIONS). Despite initially successful symptomatic treatment of the allergic symptoms, when symptomatic therapy was discontinued, the allergic symptoms recurred soon thereafter in some patients without further azithromycin exposure. These patients required prolonged periods of observation and symptomatic treatment. The relationship of these episodes to the long tissue half-life of azithromycin and subsequent prolonged exposure to antigen is unknown at present.

If an allergic reaction occurs, the drug should be discontinued and appropriate therapy should be instituted. Physicians should be aware that reappearance of the allergic symptoms may occur when symptomatic therapy is discontinued.

Clostridium difficile associated diarrhea (CDAD) has been reported with use of nearly all antibacterial agents, including azithromycin, and may range in severity from mild diarrhea to fatal colitis. Treatment with antibacterial agents alters the normal flora of the colon leading to overgrowth of C. difficile.

C. difficile produces toxins A and B which contribute to the development of CDAD. Hypertoxin producing strains of C. difficile cause increased morbidity and mortality, as these infections can be refractory to antimicrobial therapy and may require colectomy. CDAD must be considered in all patients who present with diarrhea following antibiotic use. Careful medical history is necessary since CDAD has been reported to occur over two months after the administration of antibacterial agents.

If CDAD is suspected or confirmed, ongoing antibiotic use not directed against C. difficile may need to be discontinued. Appropriate fluid and electrolyte management, protein supplementation, antibiotic treatment of C. difficile, and surgical evaluation should be instituted as clinically indicated.

PRECAUTIONS

General

Because azithromycin is principally eliminated via the liver, caution should be exercised when azithromycin is administered to patients with impaired hepatic function. Due to the limited data in subjects with GFR<10 mL/min, caution should be exercised when prescribing azithromycin in these patients. (See CLINICAL PHARMACOLOGY - Renal Insufficiency).

Prolonged cardiac repolarization and QT interval, imparting a risk of developing cardiac arrhythmia and torsades de pointes, have been seen in treatment with other macrolides. A similar effect with azithromycin cannot be completely ruled out in patients at increased risk for prolonged cardiac repolarization.

Exacerbation of symptoms of myasthenia gravis and new onset of myasthenic syndrome have been reported in patients receiving azithromycin therapy.

Prescribing azithromycin in the absence of a proven or strongly suspected bacterial infection or a prophylactic indication is unlikely to provide benefit to the patient and increases the risk of the development of drug-resistant bacteria.

Information for Patients

Azithromycin tablets may be taken with or without food. However, increased tolerability has been observed when tablets are taken with food.

Azithromycin for oral suspension in single 1 g packets can be taken with or without food after constitution.

Patients should also be cautioned not to take aluminum- and magnesium-containing antacids and azithromycin simultaneously.

The patient should be directed to discontinue azithromycin immediately and contact a physician if any signs of an allergic reaction occur.

Patients should be counseled that antibacterial drugs including azithromycin should only be used to treat bacterial infections. They do not treat viral infections (e.g., the common cold). When azithromycin is prescribed to treat bacterial infection, patients should be told that although it is common to feel better early in the course of therapy, the medication should be taken exactly as directed. Skipping doses or not completing the full course of therapy may (1) decrease the effectiveness of the immediate treatment and (2) increase the likelihood that bacteria will develop resistance and will not be treatable by azithromycin or other antibacterial drugs in the future.

Diarrhea is a common problem caused by antibiotics which usually ends when the antibiotic is discontinued. Sometimes after starting treatment with antibiotics, patients can develop watery and bloody stools (with or without stomach cramps and fever) even as late as two or more months after having taken the last dose of the antibiotic. If this occurs, patients should contact their physician as soon as possible.

Drug Interactions

Aluminum- and magnesium-containing antacids reduce the peak serum levels (rate) but not the AUC (extent) of azithromycin (500 mg) absorption.

Administration of cimetidine (800 mg) two hours prior to azithromycin had no effect on azithromycin (500 mg) absorption.

A single oral dose of 1200 mg azithromycin (2 × 600 mg azithromycin tablets) did not alter the pharmacokinetics of a single 800 mg oral dose of fluconazole in healthy adult subjects.

Total exposure (AUC) and half-life of azithromycin following the single oral tablet dose of 1200 mg were unchanged and the reduction in Cmax was not significant (mean decrease of 18%) by coadministration with 800 mg fluconazole.

A single oral dose of 1200 mg azithromycin (2 × 600 mg azithromycin tablets) had no significant effect on the pharmacokinetics of indinavir (800 mg indinavir tid for 5 days) in healthy adult subjects.

Coadministration of a single oral dose of 1200 mg azithromycin (2 × 600 mg azithromycin tablets) with steady-state nelfinavir (750 mg tid) to healthy adult subjects produced a decrease of approximately 15% in mean AUC0–8 of nelfinavir and its M8 metabolite. Mean Cmax of nelfinavir and its M8 metabolite were not significantly affected. No dosage adjustment of nelfinavir is required when nelfinavir is coadministered with azithromycin.

Coadministration of nelfinavir (750 mg tid) at steady state with a single oral dose of 1200 mg azithromycin increased the mean AUC0–∞ of azithromycin by approximately a factor of 2-times (range of up to 4 times) of that when azithromycin was given alone. The mean Cmax of azithromycin was also increased by approximately a factor of 2-times (range of up to 5 times) of that when azithromycin was given alone. Dose adjustment of azithromycin is not recommended. However, when administered in conjunction with nelfinavir, close monitoring for known side effects of azithromycin, such as liver enzyme abnormalities and hearing impairment, is warranted. (See ADVERSE REACTIONS.)

Following administration of trimethoprim/sulfamethoxazole DS (160 mg/800 mg) for 7 days to healthy adult subjects, coadministration of 1200 mg azithromycin (2 × 600 mg azithromycin tablets) on the 7th day had no significant effects on peak concentrations (Cmax), total exposure (AUC), and the urinary excretion of either trimethoprim or sulfamethoxazole.

Coadministration of trimethoprim/sulfamethoxazole DS for 7 days had no significant effect on the peak concentration (Cmax) and total exposure (AUC) of azithromycin following administration of the single 1200 mg tablet dose to healthy adult subjects.

Administration of a 600 mg single oral dose of azithromycin had no effect on the pharmacokinetics of efavirenz given at 400 mg doses for 7 days to healthy adult subjects.

Efavirenz, when administered at a dose of 400 mg for seven days produced a 22% increase in the Cmax of azithromycin administered as a 600 mg single oral dose, while the AUC of azithromycin was not affected.

Azithromycin (500 mg Day 1, 250 mg Days 2–5) did not affect the plasma levels or pharmacokinetics of theophylline administered as a single intravenous dose. The effect of azithromycin on the plasma levels or pharmacokinetics of theophylline administered in multiple doses resulting in therapeutic steady-state levels of theophylline is not known. However, concurrent use of macrolides and theophylline has been associated with increases in the serum concentrations of theophylline. Therefore, until further data are available, prudent medical practice dictates careful monitoring of plasma theophylline levels in patients receiving azithromycin and theophylline concomitantly.

Although, in a study of 22 healthy men, a 5-day course of azithromycin did not affect the prothrombin time from a subsequently administered dose of warfarin, spontaneous post-marketing reports suggest that concomitant administration of azithromycin may potentiate the effects of oral anticoagulants. Prothrombin times should be carefully monitored while patients are receiving azithromycin and oral anticoagulants concomitantly.

Dose adjustments are not indicated when azithromycin and zidovudine are coadministered. When zidovudine (100 mg q3h ×5) was coadministered with daily azithromycin (600 mg, n=5 or 1200 mg, n=7), mean Cmax, AUC and Clr increased by 26% (CV 54%), 10% (CV 26%) and 38% (CV 114%), respectively. The mean AUC of phosphorylated zidovudine increased by 75% (CV 95%), while zidovudine glucuronide Cmax and AUC increased by less than 10%. In another study, addition of 1 gram azithromycin per week to a regimen of 10 mg/kg daily zidovudine resulted in 25% (CV 70%) and 13% (CV 37%) increases in zidovudine Cmax and AUC, respectively. Zidovudine glucuronide mean Cmax and AUC increased by 16% (CV 61%) and 8.0% (CV 32%), respectively.

Doses of 1200 mg/day azithromycin for 14 days in 6 subjects increased Cmax of concurrently administered didanosine (200 mg q.12h) by 44% (54% CV) and AUC by 14% (23% CV). However, none of these changes were significantly different from those produced in a parallel placebo control group of subjects.

Preliminary data suggest that coadministration of azithromycin and rifabutin did not markedly affect the mean serum concentrations of either drug. Administration of 250 mg azithromycin daily for 10 days (500 mg on the first day) produced mean concentrations of azithromycin 1 day after the last dose of 53 ng/mL when coadministered with 300 mg daily rifabutin and 49 mg/mL when coadministered with placebo. Mean concentrations 5 days after the last dose were 23 ng/mL and 21 ng/mL in the two groups of subjects. Administration of 300 mg rifabutin for 10 days produced mean concentrations of rifabutin one half day after the last dose of 60 mg/ml when coadministered with daily 250 mg azithromycin and 71 ng/mL when coadministered with placebo. Mean concentrations 5 days after the last dose were 8.1 ng/mL and 9.2 ng/mL in the two groups of subjects.

The following drug interactions have not been reported in clinical trials with azithromycin; however, no specific drug interaction studies have been performed to evaluate potential drug-drug interaction. Nonetheless, they have been observed with macrolide products. Until further data are developed regarding drug interactions when azithromycin and these drugs are used concomitantly, careful monitoring of patients is advised:

Digoxin–elevated digoxin levels.

Ergotamine or dihydroergotamine–acute ergot toxicity characterized by severe peripheral vasospasm and dysesthesia.

Triazolam–decrease the clearance of triazolam and thus may increase the pharmacologic effect of triazolam.

Drugs metabolized by the cytochrome P^450 system–elevations of serum carbamazepine, cyclosporine, hexobarbital, and phenytoin levels.

Laboratory Test Interactions

There are no reported laboratory test interactions.

Carcinogenesis, Mutagenesis, Impairment of Fertility

Long-term studies in animals have not been performed to evaluate carcinogenic potential. Azithromycin has shown no mutagenic potential in standard laboratory tests: mouse lymphoma assay, human lymphocyte clastogenic assay, and mouse bone marrow clastogenic assay.

Pregnancy

Teratogenic Effects

Pregnancy Category B

Reproduction studies have been performed in rats and mice at doses up to moderately maternally toxic dose levels (i.e., 200 mg/kg/day). These doses, based on a mg/m^2 basis, are estimated to be 4 and 2 times, respectively, the human daily dose of 500 mg.

With regard to the MAC treatment dose of 600 mg daily, on a mg/m^2/day basis, the doses in rats and mice are approximately 3.3 and 1.7 times the human dose, respectively.

With regard to the MAC prophylaxis dose of 1200 mg weekly, on a mg/m^2/day basis, the doses in rats and mice are approximately 2 and 1 times the human dose, respectively.

No evidence of impaired fertility or harm to the fetus due to azithromycin was found. There are, however, no adequate and well-controlled studies in pregnant women. Because animal reproduction studies are not always predictive of human response, azithromycin should be used during pregnancy only if clearly needed.

Nursing Mothers

It is not known whether azithromycin is excreted in human milk. Because many drugs are excreted in human milk, caution should be exercised when azithromycin is administered to a nursing woman.

Pediatric Use

In controlled clinical studies, azithromycin has been administered to pediatric patients ranging in age from 6 months to 12 years. For information regarding the use of azithromycin for oral suspension in the treatment of pediatric patients, please refer to the INDICATIONS AND USAGE and DOSAGE AND ADMINISTRATION sections of the prescribing information for azithromycin for oral suspension 100 mg/5 mL and 200 mg/5 mL bottles.

Safety in HIV-Infected Pediatric Patients

Safety and efficacy of azithromycin for the prevention or treatment of MAC in HIV-infected children have not been established. Safety data are available for 72 children 5 months to 18 years of age (mean 7 years) who received azithromycin for treatment of opportunistic infections. The mean duration of therapy was 242 days (range 3–2004 days) at doses of <1 to 52 mg/kg/day (mean 12 mg/kg/day). Adverse events were similar to those observed in the adult population, most of which involved the gastrointestinal tract. Treatment related reversible hearing impairment in children was observed in 4 subjects (5.6%). Two (2.8%) children prematurely discontinued treatment due to side effects: one due to back pain and one due to abdominal pain, hot and cold flushes, dizziness, headache, and numbness. A third child discontinued due to a laboratory abnormality (eosinophilia). The protocols upon which these data are based specified a daily dose of 10–20 mg/kg/day (oral and/or I.V.) of azithromycin.

Geriatric Use

Pharmacokinetic parameters in older volunteers (65–85 years old) were similar to those in younger volunteers (18–40 years old) for the 5-day therapeutic regimen. Dosage adjustment does not appear to be necessary for older patients with normal renal and hepatic function receiving treatment with this dosage regimen. (See CLINICAL PHARMACOLOGY.)

In multiple-dose clinical trials of oral azithromycin, 9% of patients were at least 65 years of age (458/4949) and 3% of patients (144/4949) were at least 75 years of age. No overall differences in safety or effectiveness were observed between these subjects and younger subjects, and other reported clinical experience has not identified differences in responses between the elderly and younger patients, but greater sensitivity of some older individuals cannot be ruled out.

Azithromycin 600 mg tablets contain 2.1 mg of sodium per tablet. Azithromycin for oral suspension 1 gram single-dose packets contain 37.0 mg of sodium per packet.

Geriatric Patients with Opportunistic Infections, Including Mycobacterium avium complex (MAC) Disease

Safety data are available for 30 patients (65–94 years old) treated with azithromycin at doses >300 mg/day for a mean of 207 days. These patients were treated for a variety of opportunistic infections, including MAC. The side effect profile was generally similar to that seen in younger patients, except for a higher incidence of side effects relating to the gastrointestinal system and to reversible impairment of hearing. (See DOSAGE AND ADMINISTRATION.)

ADVERSE REACTIONS

In clinical trials, most of the reported side effects were mild to moderate in severity and were reversible upon discontinuation of the drug. Approximately 0.7% of the patients from the multiple-dose clinical trials discontinued azithromycin therapy because of treatment-related side effects. Most of the side effects leading to discontinuation were related to the gastrointestinal tract, e.g., nausea, vomiting, diarrhea, or abdominal pain. Rarely but potentially serious side effects were angioedema and cholestatic jaundice.

Clinical

Multiple-dose regimen

Overall, the most common side effects in adult patients receiving a multiple-dose regimen of azithromycin were related to the gastrointestinal system with diarrhea/loose stools (5%), nausea (3%), and abdominal pain (3%) being the most frequently reported.

No other side effects occurred in patients on the multiple-dose regimen of azithromycin with a frequency greater than 1%. Side effects that occurred with a frequency of 1% or less included the following:

Cardiovascular: Palpitations, chest pain.
Gastrointestinal: Dyspepsia, flatulence, vomiting, melena, and cholestatic jaundice.
Genitourinary: Monilia, vaginitis, and nephritis.
Nervous System: Dizziness, headache, vertigo, and somnolence.
General: Fatigue.
Allergic: Rash, photosensitivity, and angioedema.

Chronic therapy with 1200 mg weekly regimen

The nature of side effects seen with the 1200 mg weekly dosing regimen for the prevention of Mycobacterium avium infection in severely immunocompromised HIV-infected patients were similar to those seen with short term dosing regimens. (See CLINICAL STUDIES.)

Chronic therapy with 600 mg daily regimen combined with ethambutol

The nature of side effects seen with the 600 mg daily dosing regimen for the treatment of Mycobacterium avium complex infection in severely immunocompromised HIV-infected patients were similar to those seen with short term dosing regimens. Five percent of patients experienced reversible hearing impairment in the pivotal clinical trial for the treatment of disseminated MAC in patients with AIDS. Hearing impairment has been reported with macrolide antibiotics, especially at higher doses. Other treatment related side effects occurring in >5% of subjects and seen at any time during a median of 87.5 days of therapy include: abdominal pain (14%), nausea (14%), vomiting (13%), diarrhea (12%), flatulence (5%), headache (5%) and abnormal vision (5%). Discontinuations from treatment due to laboratory abnormalities or side effects considered related to study drug occurred in 8/88 (9.1%) of subjects.

Single 1-gram dose regimen

Overall, the most common side effects in patients receiving a single-dose regimen of 1 gram of azithromycin were related to the gastrointestinal system and were more frequently reported than in patients receiving the multiple-dose regimen.

Side effects that occurred in patients on the single one-gram dosing regimen of azithromycin with a frequency of 1% or greater included diarrhea/loose stools (7%), nausea (5%), abdominal pain (5%), vomiting (2%), dyspepsia (1%), and vaginitis (1%).

Post-Marketing Experience

Adverse events reported with azithromycin during the post-marketing period in adult and/or pediatric patients for which a causal relationship may not be established include:

Allergic: Arthralgia, edema, urticaria, angioedema.
Cardiovascular: Arrhythmias including ventricular tachycardia, hypotension. There have been rare reports of QT prolongation and torsades de pointes.
Gastrointestinal: Anorexia, constipation, dyspepsia, flatulence, vomiting/diarrhea rarely resulting in dehydration, pseudomembranous colitis, pancreatitis, oral candidiasis and rare reports of tongue discoloration.
General: Asthenia, paresthesia, fatigue, malaise and anaphylaxis (rarely fatal).
Genitourinary: Interstitial nephritis and acute renal failure, vaginitis.
Hematopoietic: Thrombocytopenia.
Liver/Biliary: Abnormal liver function including hepatitis and cholestatic jaundice, as well as rare cases of hepatic necrosis and hepatic failure, some of which have resulted in death.
Nervous System: Convulsions, dizziness/vertigo, headache, somnolence, hyperactivity, nervousness, agitation and syncope.
Psychiatric: Aggressive reaction and anxiety.
Skin/Appendages: Pruritus, rarely serious skin reactions including erythema multiforme, Stevens Johnson Syndrome, and toxic epidermal necrolysis.
Special Senses: Hearing disturbances including hearing loss, deafness, and/or tinnitus, reports of taste/smell perversion and/or loss.

Laboratory Abnormalities

Significant abnormalities (irrespective of drug relationship) occurring during the clinical trials were reported as follows:

With an incidence of 1–2%, elevated serum creatine phosphokinase, potassium, ALT (SGPT), GGT, and AST (SGOT).

With an incidence of less than 1%, leukopenia, neutropenia, decreased platelet count, elevated serum alkaline phosphatase, bilirubin, BUN, creatinine, blood glucose, LDH, and phosphate.

When follow-up was provided, changes in laboratory tests appeared to be reversible.

In multiple-dose clinical trials involving more than 3000 patients, 3 patients discontinued therapy because of treatment-related liver enzyme abnormalities and 1 because of a renal function abnormality.

In a phase I drug interaction study performed in normal volunteers, 1 of 6 subjects given the combination of azithromycin and rifabutin, 1 of 7 given rifabutin alone and 0 of 6 given azithromycin alone developed a clinically significant neutropenia (<500 cells/mm^3).

Laboratory abnormalities seen in clinical trials for the prevention of disseminated Mycobacterium avium disease in severely immunocompromised HIV-infected patients are presented in the CLINICAL STUDIES section.

Chronic therapy (median duration: 87.5 days, range: 1–229 days) that resulted in laboratory abnormalities in >5% subjects with normal baseline values in the pivotal trial for treatment of disseminated MAC in severely immunocompromised HIV infected patients treated with azithromycin 600 mg daily in combination with ethambutol include: a reduction in absolute neutrophils to <50% of the lower limit of normal (10/52, 19%) and an increase to five times the upper limit of normal in alkaline phosphatase (3/35, 9%). These findings in subjects with normal baseline values are similar when compared to all subjects for analyses of neutrophil reductions (22/75 [29%]) and elevated alkaline phosphatase (16/80 [20%]). Causality of these laboratory abnormalities due to the use of study drug has not been established.

DOSAGE AND ADMINISTRATION

(See INDICATIONS AND USAGE.)

Azithromycin for oral suspension (single dose 1 g packet) can be taken with or without food after constitution. Not for pediatric use. For pediatric suspension, please refer to the INDICATIONS AND USAGE and DOSAGE AND ADMINISTRATION sections of the prescribing information for azithromycin for oral suspension 100 mg/5 mL and 200 mg/5 mL bottles.

Azithromycin tablets may be taken without regard to food. However, increased tolerability has been observed when tablets are taken with food.

The recommended dose of azithromycin for the treatment of non-gonococcal urethritis and cervicitis due to C. trachomatis is: a single 1 gram (1000 mg) dose of azithromycin. This dose can be administered as one single dose packet (1 g).

Prevention of Disseminated MAC Infections

The recommended dose of azithromycin for the prevention of disseminated Mycobacterium avium complex (MAC) disease is: 1200 mg taken once weekly. This dose of azithromycin may be combined with the approved dosage regimen of rifabutin.

Treatment of Disseminated MAC Infections

Azithromycin should be taken at a daily dose of 600 mg, in combination with ethambutol at the recommended daily dose of 15 mg/kg. Other antimycobacterial drugs that have shown in vitro activity against MAC may be added to the regimen of azithromycin plus ethambutol at the discretion of the physician or health care provider.

DIRECTIONS FOR ADMINISTRATION OF Azithromycin for oral suspension in the single dose packet (1 g)

The entire contents of the packet should be mixed thoroughly with two ounces (approximately 60 mL) of water. Drink the entire contents immediately; add an additional two ounces of water, mix, and drink to assure complete consumption of dosage. The single dose packet should not be used to administer doses other than 1000 mg of azithromycin. This packet not for pediatric use.

Renal Insufficiency

No dosage adjustment is recommended for subjects with renal impairment (GFR≤80mL/min). The mean AUC 0–120 was similar in subjects with GFR 10–80 mL/min compared to subjects with normal renal function, whereas it increased 35% in subjects with GFR<10mL/min compared to subjects with normal renal function. Caution should be exercised when azithromycin is administered to subjects with severe renal impairment. (See CLINICAL PHARMACOLOGY-Renal Insufficiency.)

Hepatic Insufficiency

The pharmacokinetics of azithromycin in subjects with hepatic impairment have not been established. No dosage adjustment recommendations can be made in patients with impaired hepatic function. (See CLINICAL PHARMACOLOGY-Hepatic Impairment.)

HOW SUPPLIED

Azithromycin for oral suspension is supplied in single dose packets containing azithromycin dihydrate equivalent to 1 gram of azithromycin as follows:

Boxes of 3 Single Dose Packets (1 g) NDC 54868-5938-0

Store single dose packets between 5° and 30°C (41° and 86°F).

CLINICAL STUDIES IN PATIENTS WITH ADVANCED HIV INFECTION FOR THE PREVENTION AND TREATMENT OF DISEASE DUE TO DISSEMINATED MYCOBACTERIUM AVIUM COMPLEX (MAC)

(See INDICATIONS AND USAGE)

Prevention of Disseminated MAC Disease

Two randomized, double blind clinical trials were performed in patients with CD4 counts <100 cells/µL. The first study (155) compared azithromycin (1200 mg once weekly) to placebo and enrolled 182 patients with a mean CD4 count of 35 cells/µL. The second study (174) randomized 723 patients to either azithromycin (1200 mg once weekly), rifabutin (300 mg daily) or the combination of both. The mean CD4 count was 51 cells/µL. The primary endpoint in these studies was disseminated MAC disease. Other endpoints included the incidence of clinically significant MAC disease and discontinuations from therapy for drug-related side effects.

MAC bacteremia

In trial 155, 85 patients randomized to receive azithromycin and 89 patients randomized to receive placebo met study entrance criteria. Cumulative incidences at 6, 12 and 18 months of the possible outcomes are in the following table:

Cumulative Incidence Rate, %: Placebo (n=89)
Month | MAC Free and Alive | MAC | Adverse Experience | Lost to Follow-up
6 | 69.7 | 13.5 | 6.7 | 10.1
12 | 47.2 | 19.1 | 15.7 | 18.0
18 | 37.1 | 22.5 | 18.0 | 22.5
Cumulative Incidence Rate, %: Azithromycin (n=85)
Month | MAC Free and Alive | MAC | Adverse Experience | Lost to Follow-up
6 | 84.7 | 3.5 | 9.4 | 2.4
12 | 63.5 | 8.2 | 16.5 | 11.8
18 | 44.7 | 11.8 | 25.9 | 17.6

The difference in the one year cumulative incidence rates of disseminated MAC disease (placebo–azithromycin) is 10.9%. This difference is statistically significant (p=0.037) with a 95% confidence interval for this difference of (0.8%, 20.9%). The comparable number of patients experiencing adverse events and the fewer number of patients lost to follow-up on azithromycin should be taken into account when interpreting the significance of this difference.

In trial 174, 223 patients randomized to receive rifabutin, 223 patients randomized to receive azithromycin, and 218 patients randomized to receive both rifabutin and azithromycin met study entrance criteria. Cumulative incidences at 6, 12 and 18 months of the possible outcomes are recorded in the following table:

Cumulative Incidence Rate, %: Rifabutin (n=223)
Month | MAC Free and Alive | MAC | Adverse Experience | Lost to Follow-up
6 | 83.4 | 7.2 | 8.1 | 1.3
12 | 60.1 | 15.2 | 16.1 | 8.5
18 | 40.8 | 21.5 | 24.2 | 13.5
Cumulative Incidence Rate, %: Azithromycin (n=223)
Month | MAC Free and Alive | MAC | Adverse Experience | Lost to Follow-up
6 | 85.2 | 3.6 | 5.8 | 5.4
12 | 65.5 | 7.6 | 16.1 | 10.8
18 | 45.3 | 12.1 | 23.8 | 18.8
Cumulative Incidence Rate, %: Azithromycin/Rifabutin Combination (n=218)
Month | MAC Free and Alive | MAC | Adverse Experience | Lost to Follow-up
6 | 89.4 | 1.8 | 5.5 | 3.2
12 | 71.6 | 2.8 | 15.1 | 10.6
18 | 49.1 | 6.4 | 29.4 | 15.1

Comparing the cumulative one year incidence rates, azithromycin monotherapy is at least as effective as rifabutin monotherapy. The difference (rifabutin–azithromycin) in the one year rates (7.6%) is statistically significant (p=0.022) with an adjusted 95% confidence interval (0.9%, 14.3%). Additionally, azithromycin/rifabutin combination therapy is more effective than rifabutin alone. The difference (rifabutin–azithromycin/rifabutin) in the cumulative one year incidence rates (12.5%) is statistically significant (p<0.001) with an adjusted 95% confidence interval of (6.6%, 18.4%). The comparable number of patients experiencing adverse events and the fewer number of patients lost to follow-up on rifabutin should be taken into account when interpreting the significance of this difference.

In Study 174, sensitivity testing^5 was performed on all available MAC isolates from subjects randomized to either azithromycin, rifabutin or the combination. The distribution of MIC values for azithromycin from susceptibility testing of the breakthrough isolates was similar between study arms. As the efficacy of azithromycin in the treatment of disseminated MAC has not been established, the clinical relevance of these in vitro MICs as an indicator of susceptibility or resistance is not known.

Clinically Significant Disseminated MAC Disease

In association with the decreased incidence of bacteremia, patients in the groups randomized to either azithromycin alone or azithromycin in combination with rifabutin showed reductions in the signs and symptoms of disseminated MAC disease, including fever or night sweats, weight loss and anemia.

Discontinuations From Therapy For Drug-Related Side Effects

In Study 155, discontinuations for drug-related toxicity occurred in 8.2% of subjects treated with azithromycin and 2.3% of those given placebo (p=0.121). In Study 174, more subjects discontinued from the combination of azithromycin and rifabutin (22.7%) than from azithromycin alone (13.5%; p=0.026) or rifabutin alone (15.9%; p=0.209).

Safety

As these patients with advanced HIV disease were taking multiple concomitant medications and experienced a variety of intercurrent illnesses, it was often difficult to attribute adverse events to study medication. Overall, the nature of side effects seen on the weekly dosage regimen of azithromycin over a period of approximately one year in patients with advanced HIV disease was similar to that previously reported for shorter course therapies.

INCIDENCE OF ONE OR MORE TREATMENT RELATED [Includes those events considered possibly or probably related to study drug] ADVERSE EVENTS [>2% adverse event rates for any group (except uveitis).] IN HIV INFECTED PATIENTS RECEIVING PROPHYLAXIS FOR DISSEMINATED MAC OVER APPROXIMATELY 1 YEAR
 | Study 155 |  | Study 174
 | Placebo (N=91) | Azithromycin 1200 mg weekly (N=89) | Azithromycin 1200 mg weekly (N=233) | Rifabutin 300 mg daily (N=236) | Azithromycin + Rifabutin (N=224)
Mean Duration of Therapy (days) | 303.8 | 402.9 | 315 | 296.1 | 344.4
Discontinuation of Therapy | 2.3 | 8.2 | 13.5 | 15.9 | 22.7
Autonomic Nervous System
Mouth Dry | 0 | 0 | 0 | 3.0 | 2.7
Central Nervous System
Dizziness | 0 | 1.1 | 3.9 | 1.7 | 0.4
Headache | 0 | 0 | 3.0 | 5.5 | 4.5
Gastrointestinal
Diarrhea | 15.4 | 52.8 | 50.2 | 19.1 | 50.9
Loose Stools | 6.6 | 19.1 | 12.9 | 3.0 | 9.4
Abdominal Pain | 6.6 | 27 | 32.2 | 12.3 | 31.7
Dyspepsia | 1.1 | 9 | 4.7 | 1.7 | 1.8
Flatulence | 4.4 | 9 | 10.7 | 5.1 | 5.8
Nausea | 11 | 32.6 | 27.0 | 16.5 | 28.1
Vomiting | 1.1 | 6.7 | 9.0 | 3.8 | 5.8
General
Fever | 1.1 | 0 | 2.1 | 4.2 | 4.9
Fatigue | 0 | 2.2 | 3.9 | 2.1 | 3.1
Malaise | 0 | 1.1 | 0.4 | 0 | 2.2
Musculoskeletal
Arthralgia | 0 | 0 | 3.0 | 4.2 | 7.1
Psychiatric
Anorexia | 1.1 | 0 | 2.1 | 2.1 | 3.1
Skin & Appendages
Pruritus | 3.3 | 0 | 3.9 | 3.4 | 7.6
Rash | 3.2 | 3.4 | 8.1 | 9.4 | 11.1
Skin discoloration | 0 | 0 | 0 | 2.1 | 2.2
Special Senses
Tinnitus | 4.4 | 3.4 | 0.9 | 1.3 | 0.9
Hearing Decreased | 2.2 | 1.1 | 0.9 | 0.4 | 0
Uveitis | 0 | 0 | 0.4 | 1.3 | 1.8
Taste Perversion | 0 | 0 | 1.3 | 2.5 | 1.3

Side effects related to the gastrointestinal tract were seen more frequently in patients receiving azithromycin than in those receiving placebo or rifabutin. In Study 174, 86% of diarrheal episodes were mild to moderate in nature with discontinuation of therapy for this reason occurring in only 9/233 (3.8%) of patients.

Changes in Laboratory Values

In these immunocompromised patients with advanced HIV infection, it was necessary to assess laboratory abnormalities developing on study with additional criteria if baseline values were outside the relevant normal range.

Prophylaxis Against Disseminated MAC Abnormal Laboratory Values [excludes subjects outside of the relevant normal range at baseline]
 |  | Placebo |  | Azithromycin 1200 mg weekly |  | Rifabutin 300 mg daily |  | Azithromycin & Rifabutin
Hemoglobin | <8 g/dl | 1/51 | 2% | 4/170 | 2% | 4/114 | 4% | 8/107 | 8%
Platelet Count | <50 × 10^3/mm^3 | 1/71 | 1% | 4/260 | 2% | 2/182 | 1% | 6/181 | 3%
WBC Count | <1 × 10^3/mm^3 | 0/8 | 0% | 2/70 | 3% | 2/47 | 4% | 0/43 | 0%
Neutrophils | <500/mm^3 | 0/26 | 0% | 4/106 | 4% | 3/82 | 4% | 2/78 | 3%
SGOT | >5 × ULN [=Upper Limit of Normal] | 1/41 | 2% | 8/158 | 5% | 3/121 | 3% | 6/114 | 5%
SGPT | >5 × ULN | 0/49 | 0% | 8/166 | 5% | 3/130 | 2% | 5/117 | 4%
Alk Phos | >5 × ULN | 1/80 | 1% | 4/247 | 2% | 2/172 | 1% | 3/164 | 2%

Treatment of Disseminated MAC Disease

One randomized, double blind clinical trial (Study 189) was performed in patients with disseminated MAC. In this trial, 246 HIV infected patients with disseminated MAC received either azithromycin 250 mg qd (N=65), azithromycin 600 mg qd (N=91) or clarithromycin 500 mg bid (N=90), each administered with ethambutol 15 mg/kg qd, for 24 weeks. Patients were cultured and clinically assessed every 3 weeks through week 12 and monthly thereafter through week 24. After week 24, patients were switched to any open label therapy at the discretion of the investigator and followed every 3 months through the last follow up visit of the trial. Patients were followed from the baseline visit for a period of up to 3.7 years (median: 9 months). MAC isolates recovered during study treatment or post-treatment were obtained whenever possible.

The primary endpoint was sterilization by week 24. Sterilization was based on data from the central laboratory, and was defined as two consecutive observed negative blood cultures for MAC, independent of missing culture data between the two negative observations. Analyses were performed on all randomized patients who had a positive baseline culture for MAC.

The azithromycin 250 mg arm was discontinued after an interim analysis at 12 weeks showed a significantly lower clearance of bacteremia compared to clarithromycin 500 mg bid.

Efficacy results for the azithromycin 600 mg qd and clarithromycin 500 mg bid treatment regimens are described in the following table:

Response to therapy of patients taking ethambutol and either azithromycin 600 mg qd or clarithromycin 500 mg bid
 | Azithromycin 600 mg qd | Clarithromycin 500 mg bid | [[95% confidence interval] on difference in rates (azithromycin-clarithromycin)] 95.1% CI on difference
Patients with positive culture at baseline | 68 | 57
Week 24
Two consecutive negative blood cultures [Primary endpoint] | 31/68 (46%) | 32/57 (56%) | [-28, 7]
Mortality | 16/68 (24%) | 15/57 (26%) | [-18, 13]

The primary endpoint, rate of sterilization of blood cultures (two consecutive negative cultures) at 24 weeks, was lower in the azithromycin 600 mg qd group than in the clarithromycin 500 mg bid group.

Sterilization by Baseline Colony Count

Within both treatment groups, the sterilization rates at week 24 decreased as the range of MAC cfu/mL increased.

 | Azithromycin 600 mg (N=68) | Clarithromycin 500 mg bid (N=57)
Groups Stratified by MAC Colony Counts at Baseline | No. (%) Subjects in Stratified Group Sterile at Week 24 | No. (%) Subjects in Stratified Group Sterile at Week 24
≤ 10 cfu/mL | 10/15 (66.7%) | 12/17 (70.6%)
11–100 cfu/mL | 13/28 (46.4%) | 13/19 (68.4%)
101–1,000 cfu/mL | 7/19 (36.8%) | 5/13 (38.5%)
1,001–10,000 cfu/mL | 1/5 (20.0%) | 1/5 (20%)
>10,000 cfu/mL | 0/1 (0.0%) | 1/3 (33.3%)

Susceptibility Pattern of MAC Isolates

Susceptibility testing was performed on MAC isolates recovered at baseline, at the time of breakthrough on therapy or during post-therapy follow-up. The T100 radiometric broth method was employed to determine azithromycin and clarithromycin MIC values. Azithromycin MIC values ranged from <4 to >256 µg/mL and clarithromycin MICs ranged from <1 to >32 µg/mL. The individual MAC susceptibility results demonstrated that azithromycin MIC values could be 4 to 32 fold higher than clarithromycin MIC values.

During study treatment and post-treatment follow up for up to 3.7 years (median: 9 months) in study 189, a total of 6/68 (9%) and 6/57 (11%) of the patients randomized to azithromycin 600 mg daily and clarithromycin 500 mg bid, respectively, developed MAC blood culture isolates that had a sharp increase in MIC values. All twelve MAC isolates had azithromycin MIC's ≥256 µg/mL and clarithromycin MIC's >32 µg/mL. These high MIC values suggest development of drug resistance. However, at this time, specific breakpoints for separating susceptible and resistant MAC isolates have not been established for either macrolide.

ANIMAL TOXICOLOGY

Phospholipidosis (intracellular phospholipid binding) has been observed in some tissues of mice, rats, and dogs given multiple doses of azithromycin. It has been demonstrated in numerous organ systems (e.g., eye, dorsal root ganglia, liver, gallbladder, kidney, spleen, and pancreas) in dogs administered doses which, based on pharmacokinetics, are as low as 2 times greater than the recommended adult human dose and in rats at doses comparable to the recommended adult human dose. This effect has been reversible after cessation of azithromycin treatment. The significance of these findings for humans is unknown.

REFERENCES

1. National Committee for Clinical Laboratory Standards. Methods for Dilution Antimicrobial Susceptibility Tests for Bacteria that Grow Aerobically–Third Edition. Approved Standard NCCLS Document M7-A3, Vol. 13, No. 25, NCCLS, Villanova, PA, December 1993.
2. National Committee for Clinical Laboratory Standards. Performance Standards for Antimicrobial Disk Susceptibility Tests–Fifth Edition. Approved Standard NCCLS Document M2-A5, Vol. 13, No. 24, NCCLS, Villanova, PA, December 1993.
3. Dunne MW, Foulds G, Retsema JA. Rationale for the use of azithromycin as Mycobacterium avium chemoprophylaxis. American J Medicine 1997; 102(5C):37–49.
4. Meier A, Kirshner P, Springer B, et al. Identification of mutations in 23S rRNA gene of clarithromycin-resistant Mycobacterium intracellulare. Antimicrob Agents Chemother. 1994;38:381–384.
5. Methodology per Inderlied CB, et al. Determination of In Vitro Susceptibility of Mycobacterium avium Complex Isolates to Antimicrobial Agents by Various Methods. Antimicrob Agents Chemother 1987; 31:1697–1702.

Rx only

LAB-0302-6.0
January 2009

Additional barcode labeling by:
Physicians Total Care, Inc.
Tulsa, Oklahoma 74146

PRINCIPAL DISPLAY PANEL

azithromycin
for oral suspension

one gram*
single dose packet

contains
ONE DOSE REGIMEN

Rx only

NDC 54868-5938-0